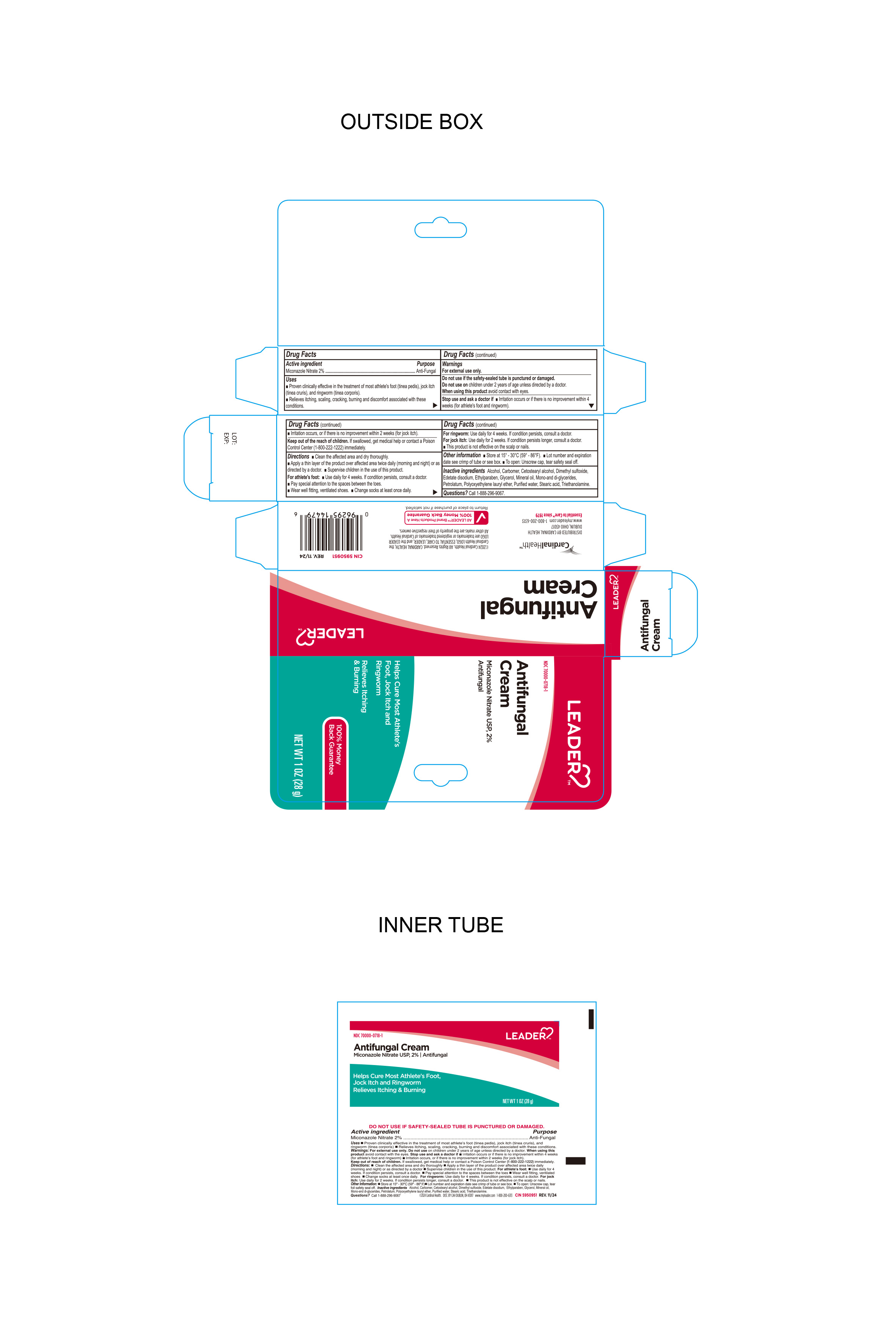 DRUG LABEL: MICONAZOLE Nitrate 2% Cream ANTIFUNGAL
NDC: 70000-0718 | Form: CREAM
Manufacturer: Cardinal Health 110 dba LEADER
Category: otc | Type: HUMAN OTC DRUG LABEL
Date: 20250513

ACTIVE INGREDIENTS: MICONAZOLE NITRATE 2 g/100 g
INACTIVE INGREDIENTS: SODIUM LAURETH-4 PHOSPHATE; GLYCERYL MONO AND DIPALMITOSTEARATE; ETHYLPARABEN; ALCOHOL; CARBOMER; CETOSTEARYL ALCOHOL; DIMETHYL SULFOXIDE; EDETATE DISODIUM; GLYCERIN; MINERAL OIL; WATER; STEARIC ACID; TROLAMINE; PETROLATUM

Leader Antifungal Cream

Active ingredient

Miconazole Nitrate 2%

Purpose

Anti-Fungal

Keep out of reach of children.If swallowed, get medical help or contact a Poison Control Center (1-800-222-1222) immediately.

Uses

- proven clinically effective in the treatment of most athlete's foot (tinea pedis), jock itch (tinea crurus), and ringworm (tinea capitis)
- relieves itching, scaling, cracking, burning and discomfort associated with these conditions.

Directions

Directions: Clean the affected area and dry thoroughly

- Apply a thin layer of the product over the affected area twice daily, morning and night or as directed by a doctor.
- Supervise children in the use of this product

For Athletes Foot

- Use daily for 4 weeks. If condition persists, consult a doctor
- Pay special Attention to the spaces between the toes
- Wear well fitting, ventilated shoes
- Change socks at least once daily

For Ringworm

- Use daily for 4 weeks. If condition persists, consult a doctor

For Jock Itch

- Use Daily for 2 weeks. If condition persists longer, consult a doctor.

This product is not effective on scalp and nails

Warnings

For external use only. Do not use if the safety-sealed tube is punctured or damaged.

Do not useon children under 2 years of age unless directed by a doctor.

When using this product avoid contact with the eyes.

Stop use and ask a doctor • irritation occurs or if there is no improvement within 4 weeks (for athlete's foot and ringworm)

If irritation occurs or if there is no improvement within 2 weeks (for Jock Itch).

INACTIVE INGREDIENT

Inactive ingredients: Alcohol, Carbomer, cetostearyl alcohol, dimethyl sulfoxide, edetate disodium, ethylparaben, glycerol, Mineral Oil, Mono and di glycerides, Petrolatum, Polyoxyethylene lauryl ether, purified water, stearic acid, triethanolamine.

Other Information

• Store at 15° - 30° c (59° - 86° f) • Lot number and expiration date see crimp of tube or see box. • To open: Unscrew cap, tear safety seal off.

Distributed by:
Cardinal HealthTM
Dublin, Ohio 43017

www.myleader.com

1-800-200-6313

Essential to Care ™ since 1979

©2024 Cardinal Health. All rights reserved. CARDINAL HEALTH, the Cardinal Health LOGO, ESSENTIAL TO CARE, LEADER, and the LEADER LOGO, are trademarks or registered trademarks of Cardinal Health. All other marks are the property of their respective owners.

All Leader Brand Products have a 100% money back guarantee.

Return to place of purchase of not satisfied.